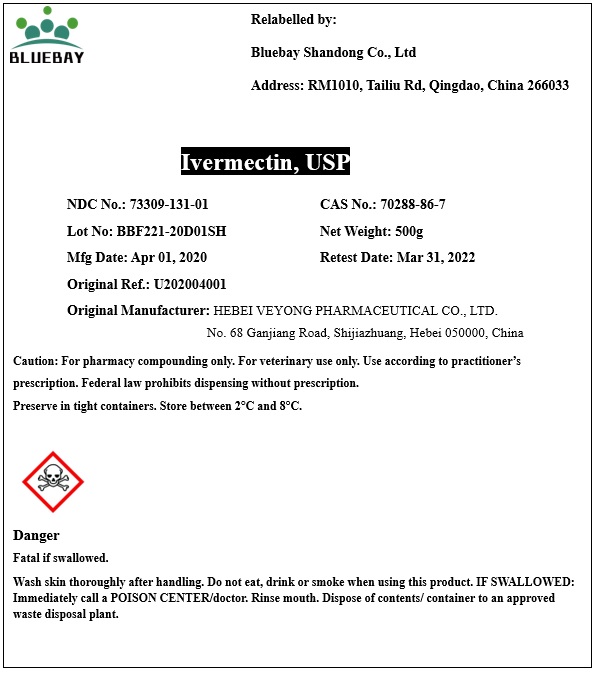 DRUG LABEL: Ivermectin
NDC: 73309-131 | Form: POWDER
Manufacturer: BLUEBAY SHANDONG CO.,LTD
Category: other | Type: BULK INGREDIENT
Date: 20200521

ACTIVE INGREDIENTS: IVERMECTIN 1 g/1 g

Ivermectin